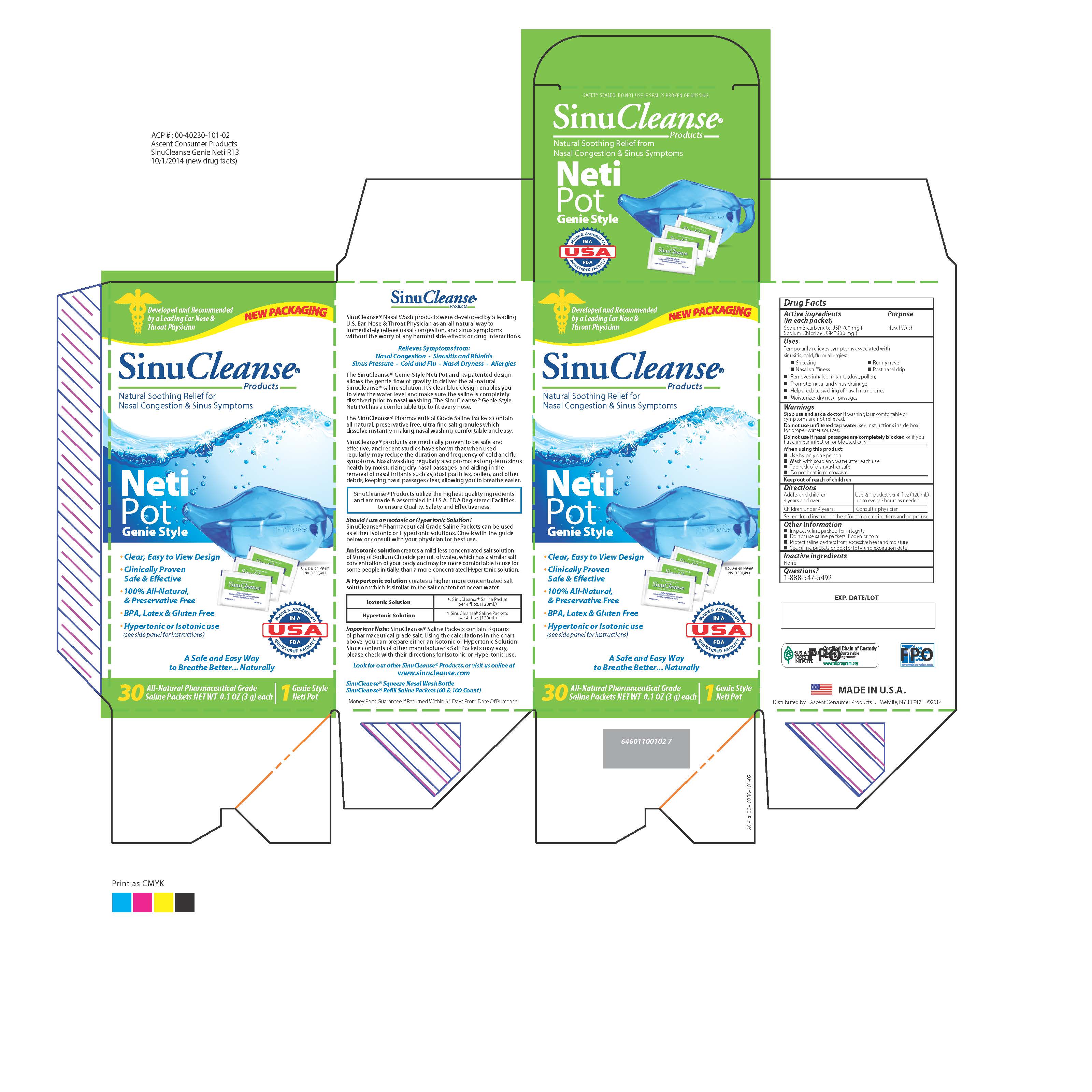 DRUG LABEL: SinuCleanse Neti-Pot
NDC: 42829-402 | Form: KIT | Route: NASAL
Manufacturer: ASCENT CONSUMER PRODUCTS, INC.
Category: otc | Type: HUMAN OTC DRUG LABEL
Date: 20250131

ACTIVE INGREDIENTS: SODIUM CHLORIDE 2300 mg/3000 mg; SODIUM BICARBONATE 700 mg/3000 mg
INACTIVE INGREDIENTS: WATER

Purpose

Nasal Wash

Uses

Temporarily relieves symptoms associated with

sinusitis, cold, flu or allergies

-Sneezing

-Nasal Stuffiness

-Runny nose

-Post nasal drip

Removes inhaled irritants (dust, pollen)

Removes nasal and sinus drainage

Helps reduce swelling of nasal membranes

Moisturizes dry nasal passages

Keep out of reach of children

Warnings

Stop use and ask a doctor if washing is uncomfortable

or symptoms are not relieved.

Do not use unfiltered tap water. see instructions inside box for proper water sources

Do not use if nasal passages are completely blocked or if you have an ear infection or blocked ears.

Directions

Adults and children 4 years and over: Use 1-2 packets per 8 fl oz (240 mL) up to every 2 hours as needed.

Children under 4 years: Consult a physician

See enclosed instruction sheet for complete directions and proper use.

Other Information

-Inspect saline packets for integrity

-Do not use saline packets if open or torn

-Protect saline packets from excessive heat and moisture

-See saline packets or box for lot number and expiration date

Questions?

1-888-547-5492

Active ingredients

(in each packet)

Sodium Bicarbonate USP (700 mg)

Sodium Chloride USP (2300 mg)

Inactive Ingredients

None

Instructions for Use of the SinuCleanse Neti Pot

Directions: Read through entire section before using for the first time.

1. Empty the contents of one SinuCleanse Saline Wash packet into the

SinuCleanse Neti Pot. First-time users should start with 1/2 packet of

the SinuCleanse dry ingredients. As you become more accustomed to

the system, work up to using 1 full packet. Additional packets may be

purchased from your nearest pharmacy.

2. Fill the pot halfway or to the middle of the indentation with a proper water source.*

This makes 1/2 cup (4 oz.) solution.

3. Stir thoroughly until dry ingredients have completely dissolved.

4. Proper head position allows solution to flow through the nose by gravity.

- Lean over the sink with your head bent down so you are looking directly into the basin.

Holding the pot in your right hand, gently insert the spout into your right nostril so that it

forms a comfortable seal.

- Rotate your head so that the right nostril is directly above the left. The forehead should

remain higher than the chin. Raise the handle of the pot so that the solution enters the right

nostril. In a few moments, the solution will begn to drain out the left nostril into the sink.

Do not inhale or "snort" solution into the nose - breathe through your mouth.

5. When the pot i empty, exhale through both nostrils to clear them

of excess mucus and solution. Gently blow your nose into a tissue.

6. Repeat the procedure on the other side.

7. Thoroughly rinse the pot after each use with water that has

been distilled, sterilized, filtered or previously boiled and leave the

pot to air dry completely. The SinuCleanse Neti Pot is top-rack dishwasher safe.